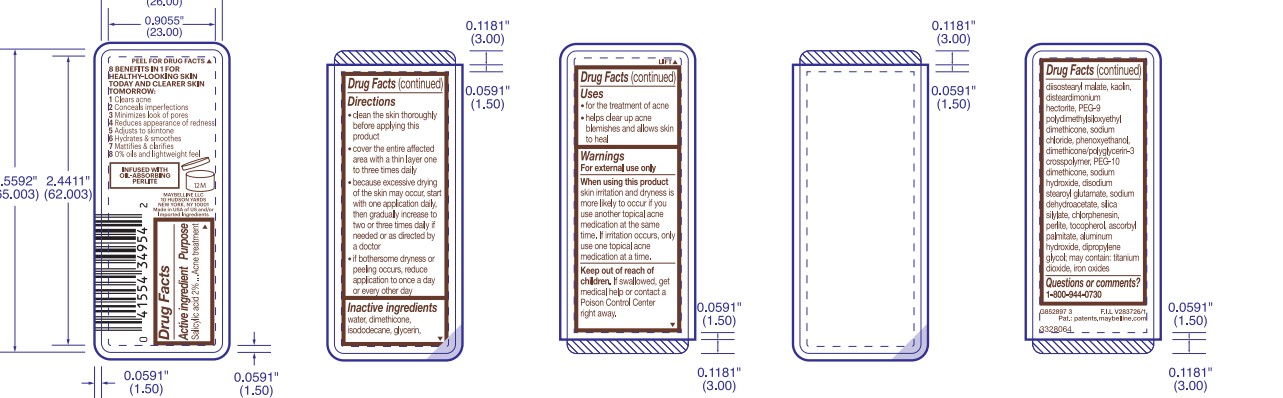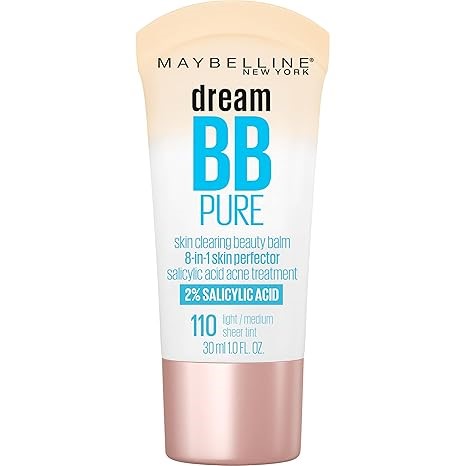 DRUG LABEL: Maybelline Dream Pure BB Beauty Balm
NDC: 49967-957 | Form: LOTION
Manufacturer: L'Oreal USA Products Inc
Category: otc | Type: HUMAN OTC DRUG LABEL
Date: 20241223

ACTIVE INGREDIENTS: Salicylic acid 20 mg/1 mL
INACTIVE INGREDIENTS: WATER; DIMETHICONE; ISODODECANE; GLYCERIN; DIISOSTEARYL MALATE; KAOLIN; DISTEARDIMONIUM HECTORITE; PEG-9 POLYDIMETHYLSILOXYETHYL DIMETHICONE; SODIUM CHLORIDE; PHENOXYETHANOL; DIMETHICONE/POLYGLYCERIN-3 CROSSPOLYMER; PEG-10 DIMETHICONE (600 CST); SODIUM HYDROXIDE; DISODIUM STEAROYL GLUTAMATE; SODIUM DEHYDROACETATE; CHLORPHENESIN; PERLITE; LUVISET 360; TOCOPHEROL; ASCORBYL PALMITATE; ALUMINUM HYDROXIDE; DIPROPYLENE GLYCOL; TITANIUM DIOXIDE; IRON OXIDES

Drug Facts

Active ingredient

Salicylic acid 2%

Purpose

Acne treatment

Uses

- for the treatment of acne

- helps clear up acne blemishes and allows skin to heal

Warnings

For external use only

When using this product

skin irritation and dryness is more likely to occur if you use another topical acne medication at the same time. If irritation occurs, only use one topical can medication at a time.

Keep out of reach of children.

If swallowed, get medical help or contact a Poison Control Center right away.

Directions

- clean the skin thoroughly before apply this product

- cover the entire affected area with a thin layer one to three times daily

- because excessive drying of the skin may occur, start with one application daily, then gradually increase to two or three times daily if needed or as directed by a doctor

- if bothersome dryness or peeling occurs, reduce application to once a day or every other day

Inactive ingredients

water, dimethicone, isododecane, glycerin, diisostearyl malate, kaolin, disteardimonium hectorite, PEG-9 polydimethylsiloxyethyl dimethicone, sodium chloride, phenoxyethanol, dimethicone/polyglycerin-3 crosspolymer, PEG-10 dimethicone, sodium hydroxide, disodium stearoyl glutamate, sodium dehydroacetate, silica silylate, chlorphenesin, perlite, acrylates copolymer, tocopherol, ascorbyl palmitate, aluminum hydroxide, PEG-9, dipropylene glycol; may contain: titanium dioxide, iron oxides

Questions or comments?

1-800-944-0730